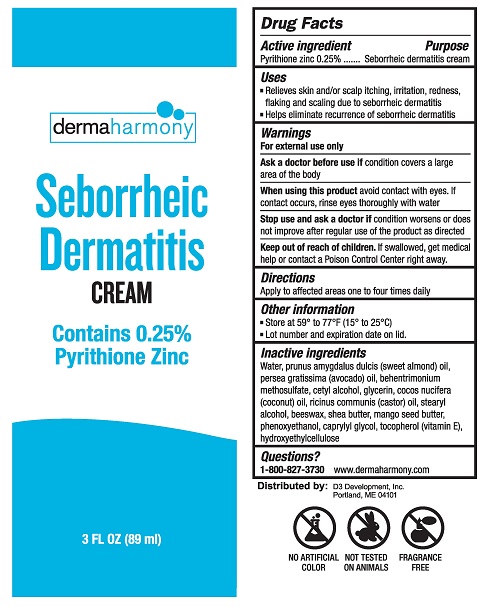 DRUG LABEL: Dermaharmony Seborrheic Dermatitis
NDC: 71819-002 | Form: CREAM
Manufacturer: D3 Development, Inc.
Category: otc | Type: HUMAN OTC DRUG LABEL
Date: 20241220

ACTIVE INGREDIENTS: PYRITHIONE ZINC 0.25 g/100 mL
INACTIVE INGREDIENTS: PHENOXYETHANOL; YELLOW WAX; GLYCERIN; CAPRYLYL GLYCOL; TOCOPHEROL; HYDROXYETHYL CELLULOSE (1800 MPA.S AT 2%); STEARYL ALCOHOL; ALMOND OIL; WATER; AVOCADO OIL; CETYL ALCOHOL; COCONUT OIL; CASTOR OIL; BEHENTRIMONIUM METHOSULFATE; SHEA BUTTER; MANGIFERA INDICA SEED BUTTER

Seborrheic Dermatitis Cream

Drug Facts

Active ingredient

Pyrithione zinc 0.25%

Purpose

Seborrheic dermatitis cream

Uses

- Relieves skin and/or scalp itching, irritation, redness, flaking and scaling due to seborrheic dermatitis
- Helps eliminate recurrence of seborrheic dermatitis

Warnings

For external use only

Ask a doctor before use ifcondition covers a large area of the body.

WHEN USING

When using this productavoid contact with eyes. If contact occurs, rinse eyes thoroughly with water

Stop use and ask a doctor ifcondition worsens or does not improve after regular use of the product as directed.

Keep out of reach of children.If swallowed, get medical help or contact a Poison Control Center right away.

Directions

Apply to affected area one to four times daily

Other information

- Store at 59° to 77°F (15° to 25°C)
- Lot number and expiration date can be found on lid.

Inactive ingredients

Water, prunus amygdalus dulcis (sweet almond) oil, persea gratissima (avocado) oil, behentrimonium methosulfate, cetyl alcohol, glycerin, coco nucifera (coconut) oil, ricinus communis (castor) oil, stearyl alcohol, beeswax, shea butter, mango seed butter, phenoxyethanol, caprylyl glycol, tocopherol (vitamin E), hydroxyethylcellulose

Questions?

1-800-827-3730

www.dermaharmony.com

Distributed by:

D3 Development, Inc.

Portland, ME 04101

PACKAGE LABEL

dermaharmony

Seborrheic Dermatitis CREAM

Contains 0.25% Pyrithione Zinc

3 FL OZ (89 ml)